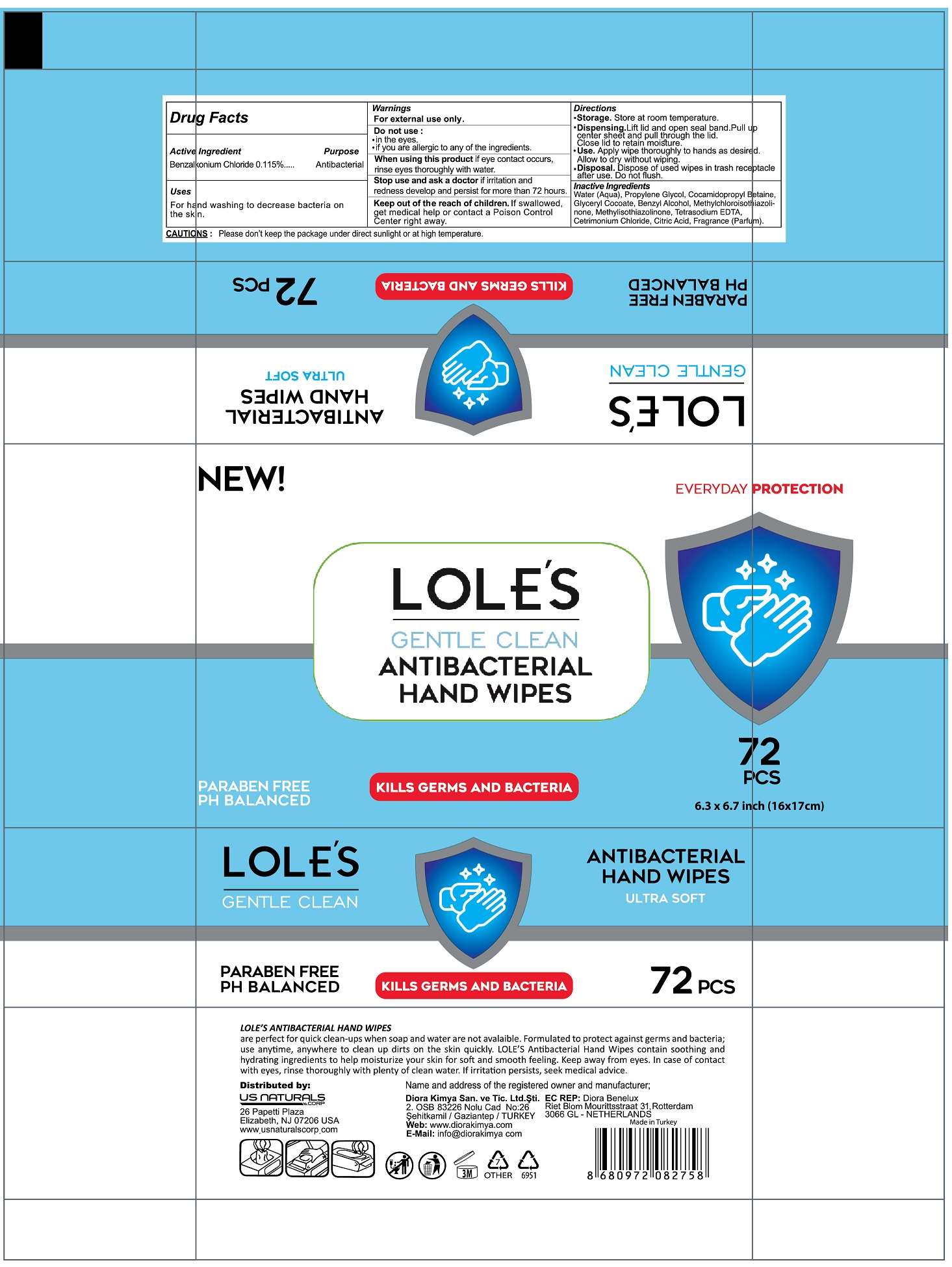 DRUG LABEL: LOLES
NDC: 73485-003 | Form: CLOTH
Manufacturer: Diora Kimya Sanayi ve Ticaret Limited Sirketi
Category: otc | Type: HUMAN OTC DRUG LABEL
Date: 20220131

ACTIVE INGREDIENTS: BENZALKONIUM CHLORIDE 0.115 g/1 1
INACTIVE INGREDIENTS: CITRIC ACID MONOHYDRATE 0.005 g/1 1; FRAGRANCE CLEAN ORC0600327 0.4 g/1 1; WATER 98.662 g/1 1; PROPYLENE GLYCOL 0.28 g/1 1; BENZYL ALCOHOL 0.184 g/1 1; CETRIMONIUM CHLORIDE 0.05 g/1 1; EDETATE SODIUM 0.01 g/1 1; METHYLCHLOROISOTHIAZOLINONE 0.0075 g/1 1; METHYLISOTHIAZOLINONE 0.0075 g/1 1; GLYCERYL COCOATE 0.186 g/1 1; COCAMIDOPROPYL BETAINE 0.093 g/1 1

Antibacterial Hand Wipes for Personal Use

Active Ingredient(s)

Benzalkonium Chloride 0.115%

Purpose: Antibacterial

Purpose

Antibacterial, Hand Wipes

Use

For hand washing to decrease bacteria on the skin.

Warnings

For external use only.

Do not use

- In the eyes
- if you are allergic to any of the ingredients.

When using this product if eye contact occurs, rinse eyes thoroughly with water.

Stop use and ask a doctor If irritation and redness develop and persist more than 72 hours.

KEEP OUT OF REACH OF CHILDREN

If swallowed, get medical help or contact a Poison Control Center right away.

Directions

Storage. Store at room temperature.

Dispensing. Lift lid and open seal band. Pull up center sheet and pull through the lid. Close lid to retain moisture.

Use. Apply wipe thoroughly to hands as desired. Allow to dry without wiping.

Disposal. Dispose of used wipes in trash receptacle after use. Do not flush.

RECENT MAJOR CHANGES

Storage. Store at room temperature.

Dispensing. Lift lid and open seal band. Pull up center sheet and pull through the lid. Close lid to retain moisture.

Use. Apply wipe thoroughly to hands as desired. Allow to dry without wiping.

Disposal. Dispose of used wipes in trash receptacle after use. Do not flush.

Other information

Storage. Store at room temperature.

Please don't keep the package under direct sunlight or at high temperature.

Inactive ingredients

Water (Aqua), Propylene Glycol, Cocoamidopropyl Betaine, Glyceryl Cocoate, Benzyl Alcohol, Methylchloroisothiazolinone, Methylisothiazolinone, Tetrasodium EDTA, Cetrimonium Chloride, Citric Acid, Fragrance (Perfum)